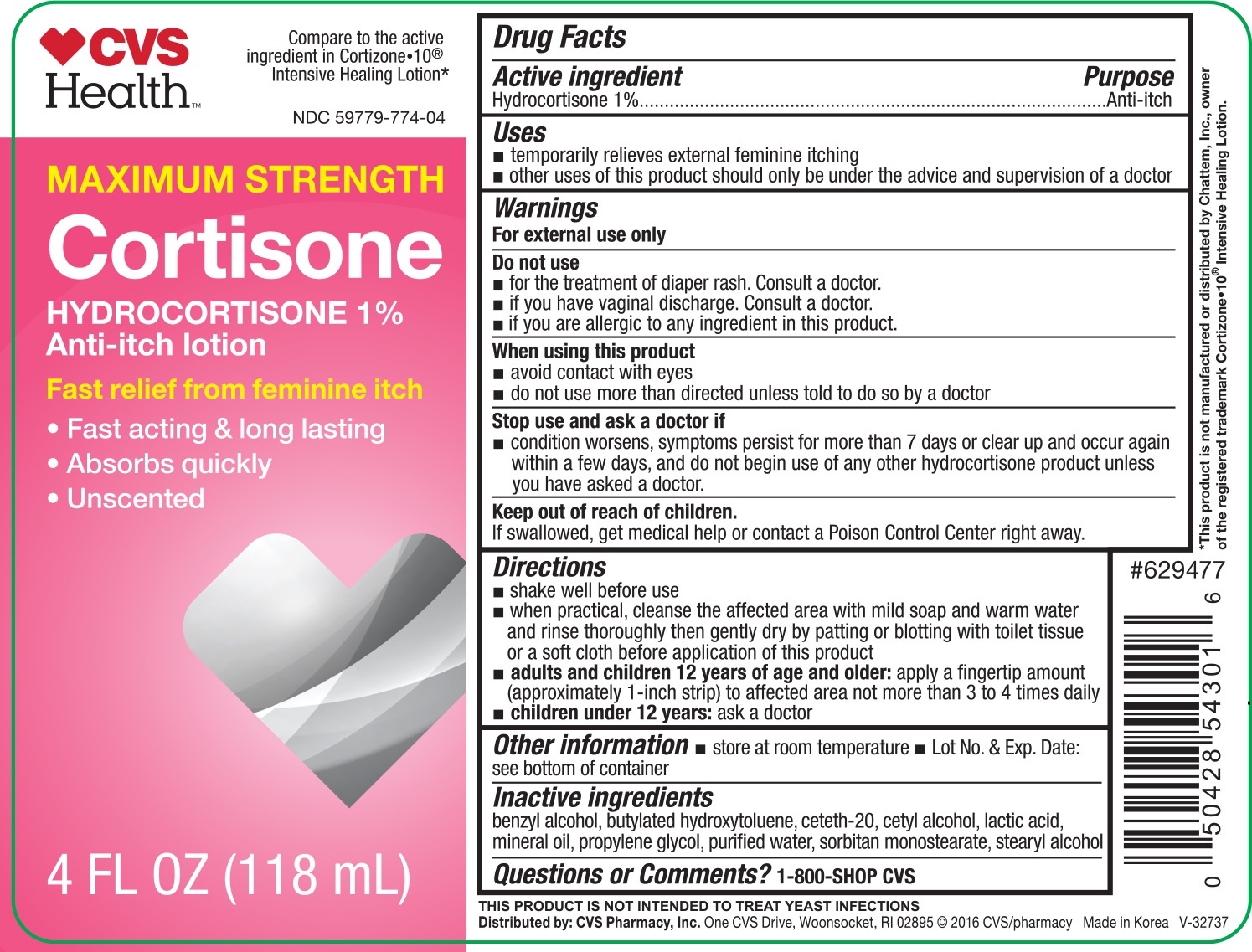 DRUG LABEL: CVS Health Maxium Strentgh Cortisone
NDC: 59779-774 | Form: LOTION
Manufacturer: CVS Pharmacy
Category: otc | Type: HUMAN OTC DRUG LABEL
Date: 20180115

ACTIVE INGREDIENTS: HYDROCORTISONE 1 mg/1 mL
INACTIVE INGREDIENTS: BENZYL ALCOHOL; BUTYLATED HYDROXYTOLUENE; CETETH-20; CETYL ALCOHOL; LACTIC ACID; MINERAL OIL; PROPYLENE GLYCOL; WATER; SORBITAN MONOSTEARATE; STEARYL ALCOHOL

CVS Feminine Hydrocortisone Anti-Itch Lotion 4 oz 54301 (2018)

Active ingredient Purpose

Hydrocortisone 1%.................................................. Anti-itch

Uses

- temporarily relieves external feminine itching
- other uses of this product should only be used under the advice and supervision of a doctor

Warnings

For external use only

Do not use

- for the treatment of diaper rash. Consult a doctor.
- if you have vaginal discharge. Consult a doctor.
- if you are allergic to any ingredient in this product.

When using this product

- avoid contact with eyes
- do not use more than directed unless told to do so by a doctor

Stop use and ask a doctor if

- condition worsens, symptoms persist for more than 7 days or clear up and occur again within a few days, and do not begin use of any other hydrocortisone product unless you have asked a doctor.

Keep out of reach of children.

If swallowed, get medical help or contact a Poison Control Center right away.

Directions

- shake well before use
- when practical, cleanse the affected area with mild soap and warm water and rinse thoroughly then gently dry by patting or blotting with toilet tissue or a soft cloth before application of this product
- adults and children 12 years of age and older: apply a fingertip amount (approxametly 1-inch strip) to affected area not more than 3 to 4 times daily
- children under 12 years: ask a doctor

Other information

- store at room temperature
- Lot No. & Exp. Date: see bottom of container

Inactive ingredients

benzyl alcohol, butylated hydroxytoluene, ceteth-20, cetyl alcohol, lactic acid, mineral oil, propylene glycol, purified water, sorbitan monostearate, stearyl alcohol

DOSAGE AND ADMINISTRATION

Distributed by:

CVS Pharmacy, Inc.

One CVS Drive

Woonsocket, RI 02895

Made in Korea